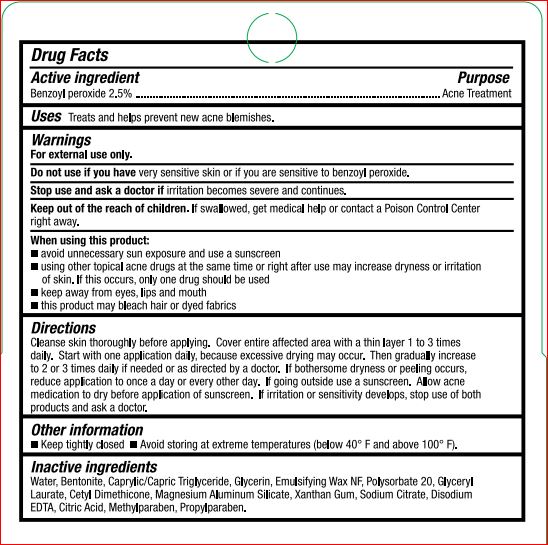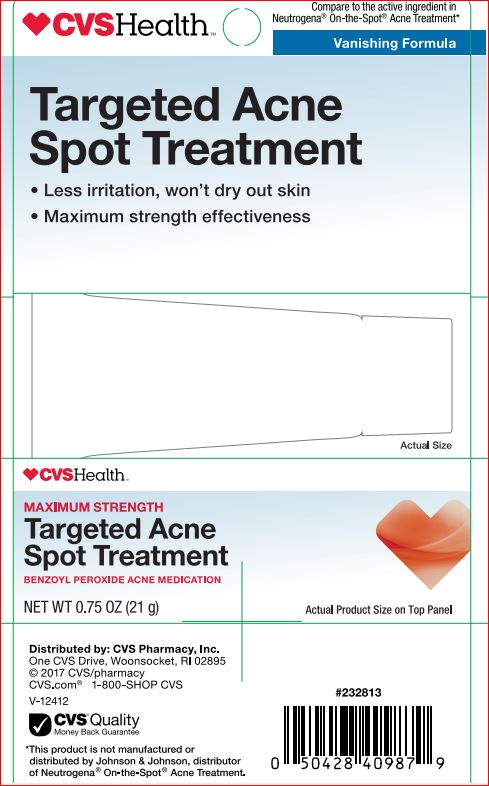 DRUG LABEL: Targeted Acne Spot Treatment
NDC: 69842-181 | Form: LOTION
Manufacturer: CVS
Category: otc | Type: HUMAN OTC DRUG LABEL
Date: 20180226

ACTIVE INGREDIENTS: BENZOYL PEROXIDE 2.50 g/100 g
INACTIVE INGREDIENTS: WATER; BENTONITE; MEDIUM-CHAIN TRIGLYCERIDES; GLYCERIN; POLYSORBATE 20; GLYCERYL LAURATE; MAGNESIUM ALUMINUM SILICATE; XANTHAN GUM; SODIUM CITRATE; EDETATE DISODIUM; ANHYDROUS CITRIC ACID; METHYLPARABEN; PROPYLPARABEN

Drug Facts

Active ingredient

Benzoyl peroxide 2.5%

Purpose

Acne Treatment

Uses

Treats and helps prevent new acne blemishes.

Warnings

For external use only.

Do not use if you have

very sensitive skin or if you are sensitive to benzoyl peroxide.

Stop use and ask a doctor if

irritation becomes severe and continues.

Keep out of reach of children.

If swallowed, get medical help or contact a Poison COntrol Center right away.

When using this product

- avoid unnecessary sun exposure and use a sunscreen
- using other topical acne drugs at the same time or right after use may increase dryness or irritation of skin. If this occurs, only one drug should be used.
- keep away from eyes, lips, mouth
- this product may bleach hair or dyed fabrics

Directions

Cleanse skin thoroughly before applying. COver entire affected area with a thin layer 1 to 3 times daily. Start with one application daily, because excessive drying may occur. Then gradually increase to 2 to 3 times daily if needed or as directed by a doctor. If bothersome dryness or peeling occurs, reduce application to once a day or every other day. If going outsie use a sunscreen. Allow acne medication to dry before application of sunscreen. If irritation or sensitivity develops, stop use of both products and ask a doctor.

Other information

- Keep tightly closed
- Avoid storing at extreme temperatures (below 40 F and above 100 F).

Inactive ingredients

Water, Bentonite, Caprylic/Capric Triglyceride, Glycerin, Emulsifying Wax NF, Polysorbate 20, Glyceryl Laurate, Cetyl Dimethicone, Magnesium Aluminum Silicate, Xanthan Gum, Sodium Citrate, Disodium EDTA, Citric Acid, Methylparaben, Propylparaben.